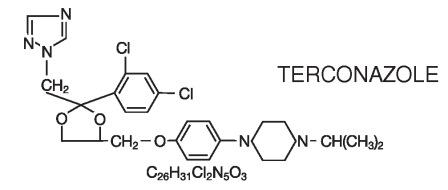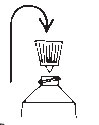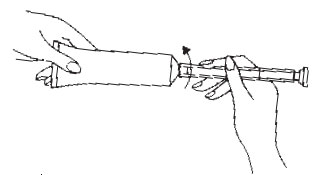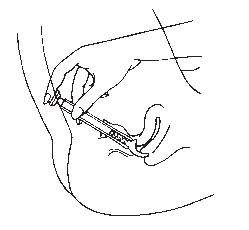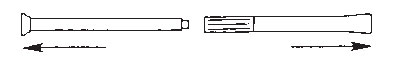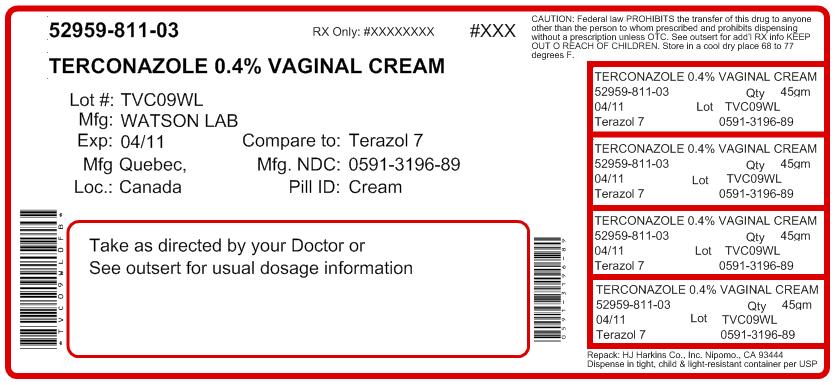 DRUG LABEL: TERCONAZOLE
NDC: 52959-811 | Form: CREAM
Manufacturer: H.J. Harkins Company, Inc.
Category: prescription | Type: HUMAN PRESCRIPTION DRUG LABEL
Date: 20120119

ACTIVE INGREDIENTS: TERCONAZOLE 4 mg/1 g
INACTIVE INGREDIENTS: BUTYLATED HYDROXYANISOLE; CETYL ALCOHOL; ISOPROPYL MYRISTATE; POLYSORBATE 60; POLYSORBATE 80; PROPYLENE GLYCOL; STEARYL ALCOHOL; WATER

TERCONAZOLE VAGINAL CREAM 0.4%
7-Day Regimen
TERCONAZOLE VAGINAL CREAM 0.4%
3-Day Regimen

description

Terconazole Vaginal Cream 0.4% is a white to off-white, water washable cream for intravaginal administration containing 0.4% of the antifungal agent terconazole, cis-1-[p-[[2-(2,4-Dichlorophenyl)-2-(1H-1,2,4-triazol-1-ylmethyl)-1,3-dioxolan-4-yl]methoxy]phenyl]-4-isopropylpiperazine, compounded in a cream base consisting of butylated hydroxyanisole, cetyl alcohol, isopropyl myristate, polysorbate 60, polysorbate 80, propylene glycol, stearyl alcohol, and purified water.

The structural formula of terconazole is as follows:

Terconazole, a triazole derivative, is a white to almost white powder with a molecular weight of 532.47. It is insoluble in water; sparingly soluble in ethanol; and soluble in butanol.

clinical pharmacology

Following intravaginal administration of terconazole in humans, absorption ranged from 5–8% in three hysterectomized subjects and 12–16% in two non-hysterectomized subjects with tubal ligations.

Following daily intravaginal administration of 0.4% terconazole 40 mg (0.4% cream x 5 g) for seven days to normal humans, plasma concentrations were low and gradually rose to a daily peak (mean of 5.9 ng/mL or 0.006 mcg/mL) at 6.6 hours.

Results from similar studies in patients with vulvovaginal candidiasis indicate that the slow rate of absorption, the lack of accumulation, and the mean peak plasma concentration of terconazole was not different from that observed in healthy women. The absorption characteristics of terconazole 0.4% in pregnant or non-pregnant patients with vulvovaginal candidiasis were also similar to those found in normal volunteers.

Following oral (30 mg) administration of ^14C-labelled terconazole, the harmonic half-life of elimination from the blood for the parent terconazole was 6.9 hours (range 4.0–11.3). Terconazole is extensively metabolized; the plasma AUC for terconazole compared to the AUC for total radioactivity was 0.6%. Total radioactivity was eliminated from the blood with a harmonic half-life of 52.2 hours (range 44–60). Excretion of radioactivity was both by renal (32–56%) and fecal (47–52%) routes.

In vitro, terconazole is highly protein bound (94.9%) and the degree of binding is independent of drug concentration.

Photosensitivity reactions were observed in some normal volunteers following repeated dermal application of terconazole 2.0% and 0.4% creams under conditions of filtered artificial ultraviolet light.

Photosensitivity reactions have not been observed in U.S. and foreign clinical trials in patients who were treated with terconazole suppositories or vaginal cream (0.4% and 0.4%).

Microbiology:

Terconazole exhibits fungicidal activity in vitro against Candida albicans. Antifungal activity has also been demonstrated against other fungi. The MIC values of terconazole against most Lactobacillus spp. typically found in the human vagina were ≥128 mcg/mL; therefore these beneficial bacteria were not affected by drug treatment.

The exact pharmacologic mode of action of terconazole is uncertain; however, it may exert its antifungal activity by the disruption of normal fungal cell membrane permeability. No resistance to terconazole has developed during successive passages of C. albicans.

indications and usage

Terconazole Vaginal Cream is indicated for the local treatment of vulvovaginal candidiasis (moniliasis). As this product is effective only for vulvovaginitis caused by the genus Candida, the diagnosis should be confirmed by KOH smears and/or cultures.

contraindications

Patients known to be hypersensitive to terconazole or to any of the components of the cream.

warnings

None.

precautions

General:

Discontinue use and do not retreat with terconazole if sensitization, irritation, fever, chills or flu-like symptoms are reported during use.

Laboratory Tests:

If there is lack of response to terconazole, appropriate microbiologic studies (standard KOH smear and/or cultures) should be repeated to confirm the diagnosis and rule out other pathogens.

Drug Interactions:

PRECAUTIONS

Terconazole Vaginal Cream 0.4%:
The therapeutic effect of this product is not affected by oral contraceptive usage.

PRECAUTIONS

Terconazole Vaginal Cream 0.4%:
The levels of estradiol (E2) and progesterone did not differ significantly when 0.4% terconazole vaginal cream was administered to healthy female volunteers established on a low dose oral contraceptive.

Carcinogenesis, Mutagenesis, Impairment of Fertility:

Carcinogenesis:
Studies to determine the carcinogenic potential of terconazole have not been performed.

CARCINOGENESIS AND MUTAGENESIS AND IMPAIRMENT OF FERTILITY

Mutagenicity:
Terconazole was not mutagenic when tested in vitro for induction of microbial point mutations (Ames test), or for inducing cellular transformation, or in vivo for chromosome breaks (micronucleus test) or dominant lethal mutations in mouse germ cells.

Impairment of Fertility:
No impairment of fertility occurred when female rats were administered terconazole orally up to 40 mg/kg/day for a three month period.

Pregnancy: Teratogenic Effects:

Teratogenic Effects

Pregnancy Category C.

There was no evidence of teratogenicity when terconazole was administered orally up to 40 mg/kg/day (50x the recommended intravaginal human dose of the 0.4% vaginal cream formulation, and 100x the intravaginal human dose of the 0.4% vaginal cream formulation) in rats, or 20 mg/kg/day in rabbits, or subcutaneously up to 20 mg/kg/day in rats.

Dosages at or below 10 mg/kg/day produced no embryotoxicity; however, there was a delay in fetal ossification at 10 mg/kg/day in rats. There was some evidence of embryotoxicity in rabbits and rats at 20-40 mg/kg. In rats, this was reflected as a decrease in litter size and number of viable young and reduced fetal weight. There was also delay in ossification and an increased incidence of skeletal variants.

The no-effect dose of 10 mg/kg/day resulted in a mean peak plasma level of terconazole in pregnant rats of 0.176 mcg/mL which exceeds by 44 times the mean peak plasma level (0.004 mcg/mL) seen in normal subjects after intravaginal administration of terconazole 0.4% vaginal cream, and by 30 times the mean peak plasma level (0.006 mcg/mL) seen in normal subjects after intravaginal administration of terconazole 0.4% vaginal cream. This safety assessment does not account for possible exposure of the fetus through direct transfer to terconazole from the irritated vagina by diffusion across amniotic membranes.

Since terconazole is absorbed from the human vagina, it should not be used in the first trimester of pregnancy unless the physician considers it essential to the welfare of the patient.

Nursing Mothers:

It is not known whether this drug is excreted in human milk. Animal studies have shown that rat offspring exposed via the milk of treated (40 mg/kg/orally) dams showed decreased survival during the first few post-partum days, but overall pup weight and weight gain were comparable to or greater than controls throughout lactation. Because many drugs are excreted in human milk, and because of the potential for adverse reaction in nursing infants from terconazole, a decision should be made whether to discontinue nursing or to discontinue the drug, taking into account the importance of the drug to the mother.

Pediatric Use:

Safety and efficacy in children have not been established.

Geriatric Use:

Clinical studies of terconazole did not include sufficient numbers of subjects aged 65 and over to determine whether they respond differently from younger subjects. Other reported clinical experience has not identified differences in responses between the elderly and younger patients.

adverse reactions

Terconazole Vaginal Cream 0.4%:

During controlled clinical studies conducted in the United States, 521 patients with vulvovaginal candidiasis were treated with terconazole 0.4% vaginal cream. Based on comparative analyses with placebo, the adverse experiences considered most likely related to terconazole 0.4% vaginal cream were headache (26% vs. 17% with placebo) and body pain (2.1% vs. 0% with placebo). Vulvovaginal burning (5.2%), itching (2.3%) or irritation (3.1%) occurred less frequently with terconazole 0.4% vaginal cream than with the vehicle placebo. Fever (1.7% vs. 0.5% with placebo) and chills (0.4% vs. 0.0% with placebo) have also been reported. The therapy-related dropout rate was 1.9%. The adverse drug experience on terconazole most frequently causing discontinuation was vulvovaginal itching (0.6%), which was lower than the incidence for placebo (0.9%).

Terconazole Vaginal Cream 0.4%:

During controlled clinical studies conducted in the United States, patients with vulvovaginal candidiasis were treated with terconazole 0.4% vaginal cream for three days. Based on comparative analyses with placebo and a standard agent, the adverse experiences considered most likely related to terconazole 0.4% vaginal cream were headache (21% vs. 16% with placebo) and dysmenorrhea (6% vs. 2% with placebo). Genital complaints in general, and burning and itching in particular, occurred less frequently in the terconazole 0.4% vaginal cream 3 day regimen (5% vs. 6%–9% with placebo). Other adverse experiences reported with terconazole 0.4% vaginal cream were abdominal pain (3.4% vs. 1% with placebo) and fever (1% vs. 0.3% with placebo). The therapy-related dropout rate was 2.0% for the terconazole 0.4% vaginal cream. The adverse drug experience most frequently causing discontinuation of therapy was vulvovaginal itching, 0.7% with the terconazole 0.4% vaginal cream group and 0.3% with the placebo group.

overdosage

Overdose of terconazole in humans has not been reported to date. In the rat, the oral LD 50 values were found to be 1741 and 849 mg/kg for the male and female, respectively. The oral LD 50 values for the male and female dog were ≅1280 and ≥640 mg/kg, respectively.

dosage and administration

Terconazole Vaginal Cream 0.4%:

One full applicator (5 g) of Terconazole Vaginal Cream (20 mg terconazole) should be administered intravaginally once daily at bedtime for seven consecutive days.

Terconazole Vaginal Cream 0.4%:

One full applicator (5 g) of Terconazole Vaginal Cream (40 mg terconazole) should be administered intravaginally once daily at bedtime for three consecutive days.

Before prescribing another course of therapy, the diagnosis should be reconfirmed by smears and/or cultures and other pathogens commonly associated with vulvovaginitis ruled out. The therapeutic effect of these products is not affected by menstruation.

how supplied

Terconazole Vaginal Cream 0.4% is available in 45 g (NDC 0591-3196-89) tubes with a measured-dose applicator. Store at Controlled Room Temperature 15° - 30° C (59° - 86° F).

Terconazole Vaginal Cream 0.4% is available in 20 g (NDC 0591-3197-52) tubes with a measured-dose applicator. Store at Controlled Room Temperature 15° - 30° C (59° - 86° F).

Mfd. for:; Watson Laboratories, Inc. Corona, CA 92880 USA | Mfd. by:; Draxis Specialty Pharmaceuticals Inc. Kirkland, Quebec, Canada H9H 4J4 or
 | JOLLC Manati, Puerto Rico 00674
Printed in U.S.A. | Revised January 2010

PATIENT INFORMATION

TERCONAZOLE Vaginal Cream 0.4%
7–Day Regimen
TERCONAZOLE Vaginal Cream 0.4%
3–Day Regimen

PATIENT INSTRUCTIONS

Filling the Applicator:

1.Remove the cap from the tube.2.Use the pointed tip on the top of the cap to puncture the seal on the tube.3.Screw the applicator onto the tube.4.Squeeze the tube from the bottom and fill the applicator until the plunger stops.5.Unscrew the applicator from the tube.

Using the Applicator:

1.Lie on your back with your knees drawn up toward your chest.2.Holding the applicator by the ribbed end of the barrel, insert the filled applicator into the vagina as far as it will comfortably go.3.Slowly press the plunger of the applicator to release the cream into the vagina.4.Remove the applicator from the vagina.5.Apply one applicatorful each night for as many days at bedtime, as directed by your doctor.

Cleaning the Applicator:

After each use, you should thoroughly clean the applicator by following the procedure below:

1.Pull the plunger out of the barrel.2.Wash the pieces with lukewarm, soapy water, and dry them thoroughly.3.Put the applicator back together by gently pushing the plunger into the barrel as far as it will go.

NOTE: Store the cream at Controlled Room Temperature 15–30°C (59–86°F). See end flap for lot number and expiration date.

A WORD ABOUT YEAST INFECTIONS

Why Do Yeast Infections Occur?

Yeast infections are caused by an organism called Candida (KAN di duh). It may be present in small and harmless amounts in the mouth, digestive tract, and vagina. Sometimes the natural balance of the vagina becomes upset. This may lead to rapid growth of Candida, which results in a yeast infection. Symptoms of a yeast infection include itching, burning, redness, and an abnormal discharge.

Your doctor can make the diagnosis of a yeast infection by evaluating your symptoms and looking at a sample of the discharge under the microscope.

How Can I Prevent Yeast Infections?

Certain factors may increase your chance of developing a yeast infection. These factors don't actually cause the problem, but they may create a situation that allows the yeast to grow rapidly.

- Clothing: Tight jeans, nylon underwear, pantyhose, and wet bathing suits can hold in heat and moisture (two conditions in which yeast organisms thrive). Looser pants or skirts, 100% cotton underwear, and stockings may help avoid this problem.
- Diet: Cutting down on sweets, milk products, and artificial sweeteners may reduce the risk of yeast infections.
- Antibiotics: Antibiotics work by eliminating disease-causing organisms. While they are helpful in curing other problems, antibiotics may lead to an overgrowth of Candida in the vagina.
- Pregnancy: Hormonal changes in the body during pregnancy encourage the growth of yeast. This is a very common time for an infection to occur. Until the baby is born, it may be hard to completely eliminate yeast infections. If you believe you are pregnant, tell your doctor.
- Menstruation: Sometimes monthly changes in hormone levels may lead to yeast infections.
- Diabetes: In addition to heat and moisture, yeast thrives on sugar. Because diabetics often have sugar in their urine, their vaginas are rich in this substance. Careful control of diabetes may help prevent yeast infection.

Controlling these factors can help eliminate yeast infections and may prevent them from coming back.

Some Other Helpful Tips:

1.For best results, be sure to use the medication as prescribed by your doctor, even if you feel better quickly.2.Avoid sexual intercourse, if your doctor advises you to do so. 3.If your partner has any penile itching, redness, or discomfort, he should consult his physician and mention that you are being treated for a yeast infection.4.You can use the medication even if you are having your menstrual period. However, you should not use tampons because they may absorb the medication. Instead, use external pads or napkins until you have finished your medication. You may also wish to wear a sanitary napkin if the vaginal medication leaks.5.Dry the genital area thoroughly after showering, bathing, or swimming. Change out of a wet bathing suit or damp exercise clothes as soon as possible. A dry environment is less likely to encourage the growth of yeast.6.Wipe from front to rear (away from the vagina) after a bowel movement.7.Don't douche unless your doctor specifically tells you to do so. Douching may disturb the vaginal balance.8.Don't scratch if you can help it. Scratching can cause more irritation and spread the infection.9.Discuss with your physician any medication you are already taking. Certain types of medication can make your vagina more susceptible to infection.10.Eat nutritious meals to promote your general health.

Mfd. for:; Watson Laboratories, Inc. Corona, CA 92880 USA | Mfd. by:; Draxis Specialty Pharmaceuticals Inc. Kirkland, Quebec, Canada H9H 4J4 or
 | JOLLC Manati, Puerto Rico 00674
Printed in U.S.A. | Revised January 2010

Repacked by:
H.J. Harkins Company, Inc.
Nipomo, CA 93444

PACKAGE LABEL

PRINCIPAL DISPLAY PANEL — Terconazole Vaginal Cream 3-Day Regimen Carton (Manati)

NDC 0591-3196-89

Terconazole Vaginal Cream
3–Day Regimen
0.4%

Tube and Applicator
For Vaginal Use Only.

Watson.

Rx only

Net Wt 0.71 oz. (20 g)
Quantity by weight not by volume.